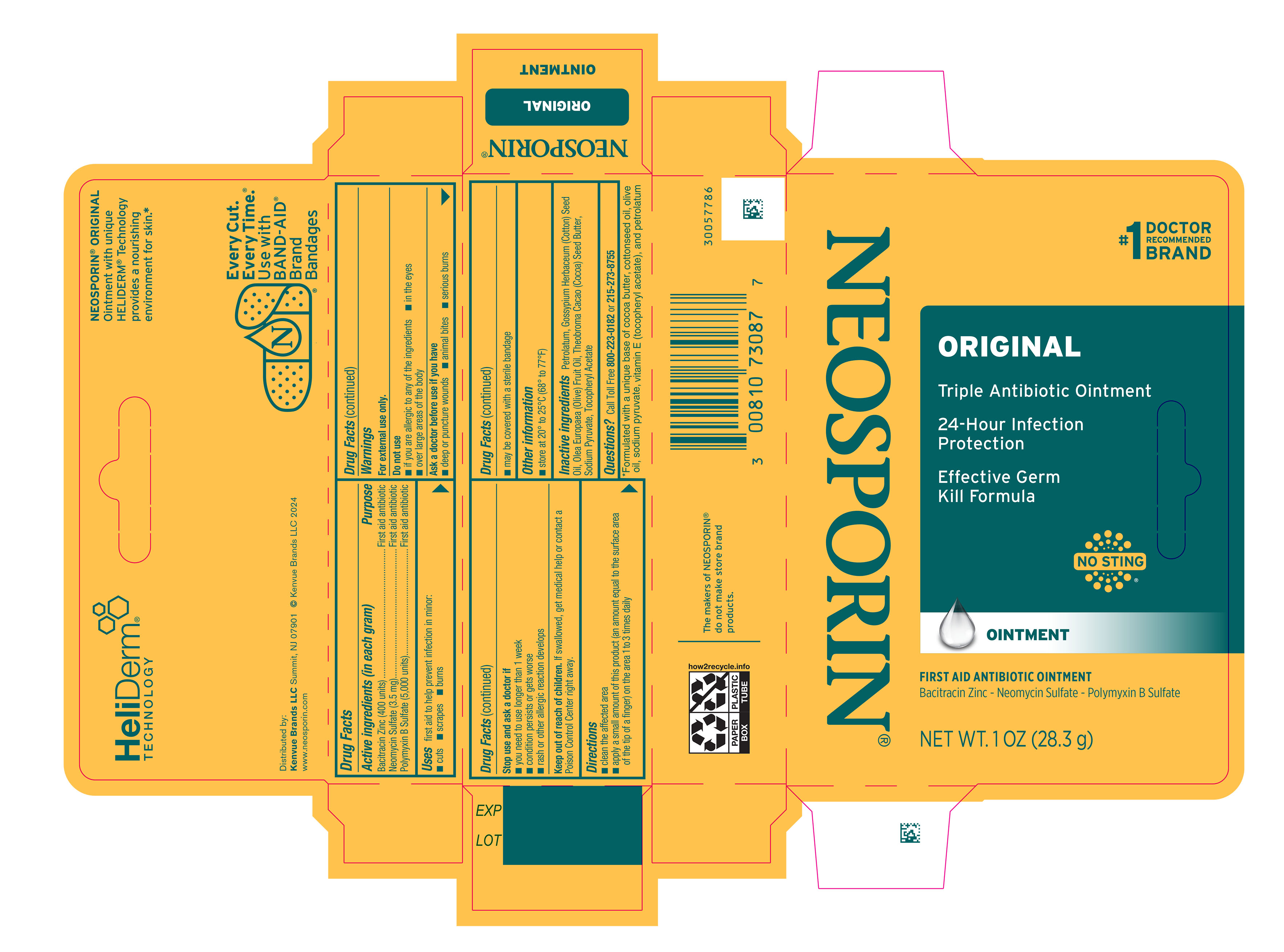 DRUG LABEL: Neosporin Original
NDC: 69968-0056 | Form: OINTMENT
Manufacturer: Kenvue Brands LLC
Category: otc | Type: HUMAN OTC DRUG LABEL
Date: 20241113

ACTIVE INGREDIENTS: BACITRACIN ZINC 400 [iU]/1 g; NEOMYCIN SULFATE 3.5 mg/1 g; POLYMYXIN B SULFATE 5000 [iU]/1 g
INACTIVE INGREDIENTS: LEVANT COTTONSEED OIL; OLIVE OIL; COCOA BUTTER; SODIUM PYRUVATE; .ALPHA.-TOCOPHEROL ACETATE; PETROLATUM

NEOSPORIN® ORIGINAL OINTMENT

Drug Facts

ACTIVE INGREDIENT

Active ingredients (in each gram) | Purpose
Bacitracin Zinc (400 units) | First aid antibiotic
Neomycin Sulfate (3.5 mg) | First aid antibiotic
Polymyxin B sulfate (5,000 units) | First aid antibiotic

Use

first aid to help prevent infection in minor:

- cuts
- scrapes
- burns

Warnings

For external use only.

Do not use

- if you are allergic to any of the ingredients
- in the eyes
- over large areas of the body

Ask a doctor before use if you have

- deep or puncture wounds
- animal bites
- serious burns

Stop use and ask a doctor if

- you need to use longer than 1 week
- condition persists or gets worse
- rash or other allergic reaction develops

Keep out of reach of children. If swallowed, get medical help or contact a Poison Control Center right away.

Directions

- clean the affected area
- apply a small amount of this product (an amount equal to the surface area of the tip of a finger) on the area 1 to 3 times daily
- may be covered with a sterile bandage

Other information

- store at 20° to 25°C (68° to 77° F)

Inactive ingredients

Petrolatum, Gossypium Herbaceum (Cotton) Seed Oil, Olea Europaea (olive) Fruit Oil, Theobroma Cacao (Cocoa) Seed Butter, Sodium Pyruvate, Tocopheryl Acetate

Questions?

Call Toll Free 800-223-0182 or 215-273-8755

Distributed by:

Kenvue Brands LLC

Summit, NJ 07901

PRINCIPAL DISPLAY PANEL - 28.3 g Tube Carton

#1
DOCTOR
RECOMMENDED
BRAND
NEOSPORIN®
ORIGINAL
Triple Antibiotic Ointment
24-Hour Infection
Protection

Effective Germ
Kill Formula

NO STING

OINTMENT

FIRST AID ANTIBIOTIC OINTMENT
Bacitracin Zinc-Neomycin Sulfate-Polymyxin B Sulfate

NET WT 1 OZ (28.3 g)